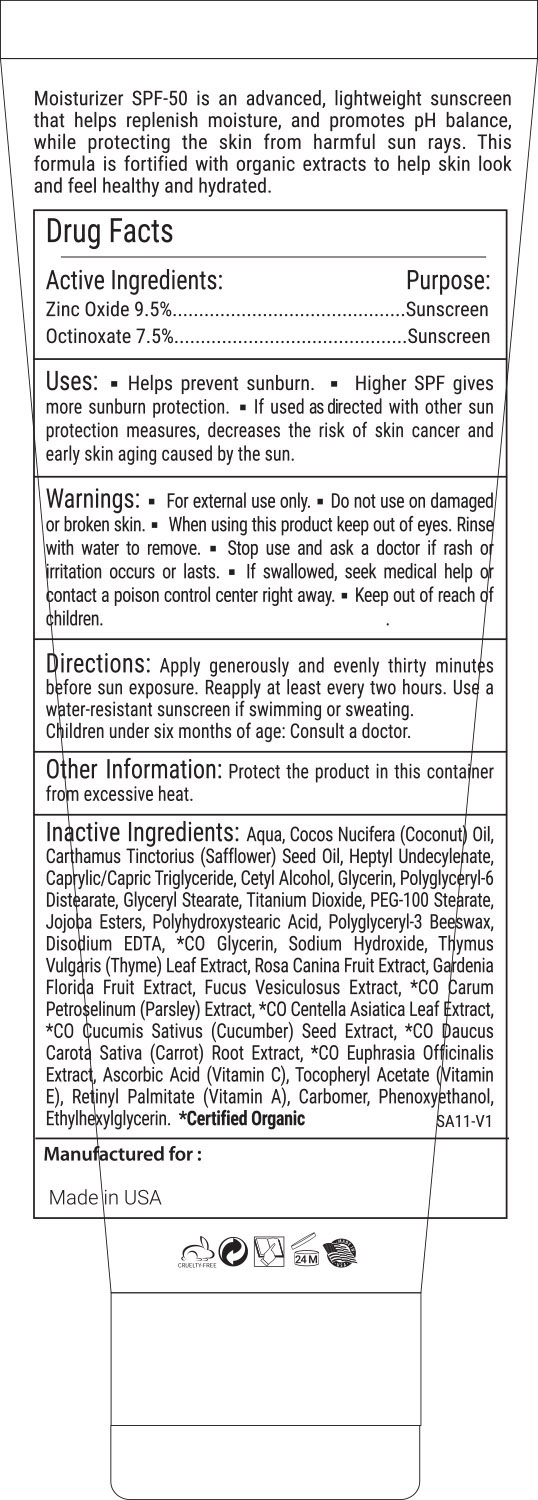 DRUG LABEL: Moisture Sunscreen SPF 50
NDC: 68062-9001 | Form: LOTION
Manufacturer: Spa de Soleil
Category: otc | Type: HUMAN OTC DRUG LABEL
Date: 20210909

ACTIVE INGREDIENTS: ZINC OXIDE 12.6 mg/120 mL; OCTINOXATE 9 mg/120 mL
INACTIVE INGREDIENTS: HEPTYL UNDECYLENATE; SAFFLOWER OIL; GLYCERIN; COCONUT OIL

Moisturizer Sunscreen SPF 50

Active Ingredients

Zinc Oxide 9.5%

Octinoxate 7.5%

Purpose

Sunscreen

Warnings

Warnings When using this product

- keep out of the eye area
- rinse with water to remove
- stop use and ask a doctor if rash or irritation develops
- for external use onlyl
- keep out of reach of children

Directions

Directions: Apply generously and evenly thirty minutes before sun exposure. Reapply at least every two hours. Use a water-resistant sunscreen if swimming or sweating.

Children under six months of age: Consult a doctor.

Inactive Ingredients

Aqua, Cocos Nucifera (Coconut) Oil, Carthamus Tinctorius (Safflower) Seed Oil, Heptyl Undecylenate, Caprylic/Capric Triglyceride, Cetyl Alcohol, Glycerin, Polyglyceryl-6 Distearate, Glyceryl Stearate, Titanium Dioxide, PEG-100 Stearate, Jojoba Esters, Polyhydroxystearic Acid, Polyglyceryl-3 Beeswax, Disodium EDTA, *CO Glycerin, Sodium Hydroxide, Thymus Vulgaris (Thyme) Leaf Extract, Rosa Canina Fruit Extract, Gardenia Florida Fruit Extract, Fucus Vesiculosus Extract, *CO Carum Petroselinum (Parsley) Extract, *CO Centella Asiatica Leaf Extract, *CO Cucumis Sativus (Cucumber) Seed Extract, *CO Daucus Carota Sativa (Carrot) Root Extract, *CO Euphrasia Officinalis Extract, Ascorbic Acid (Vitamin C),